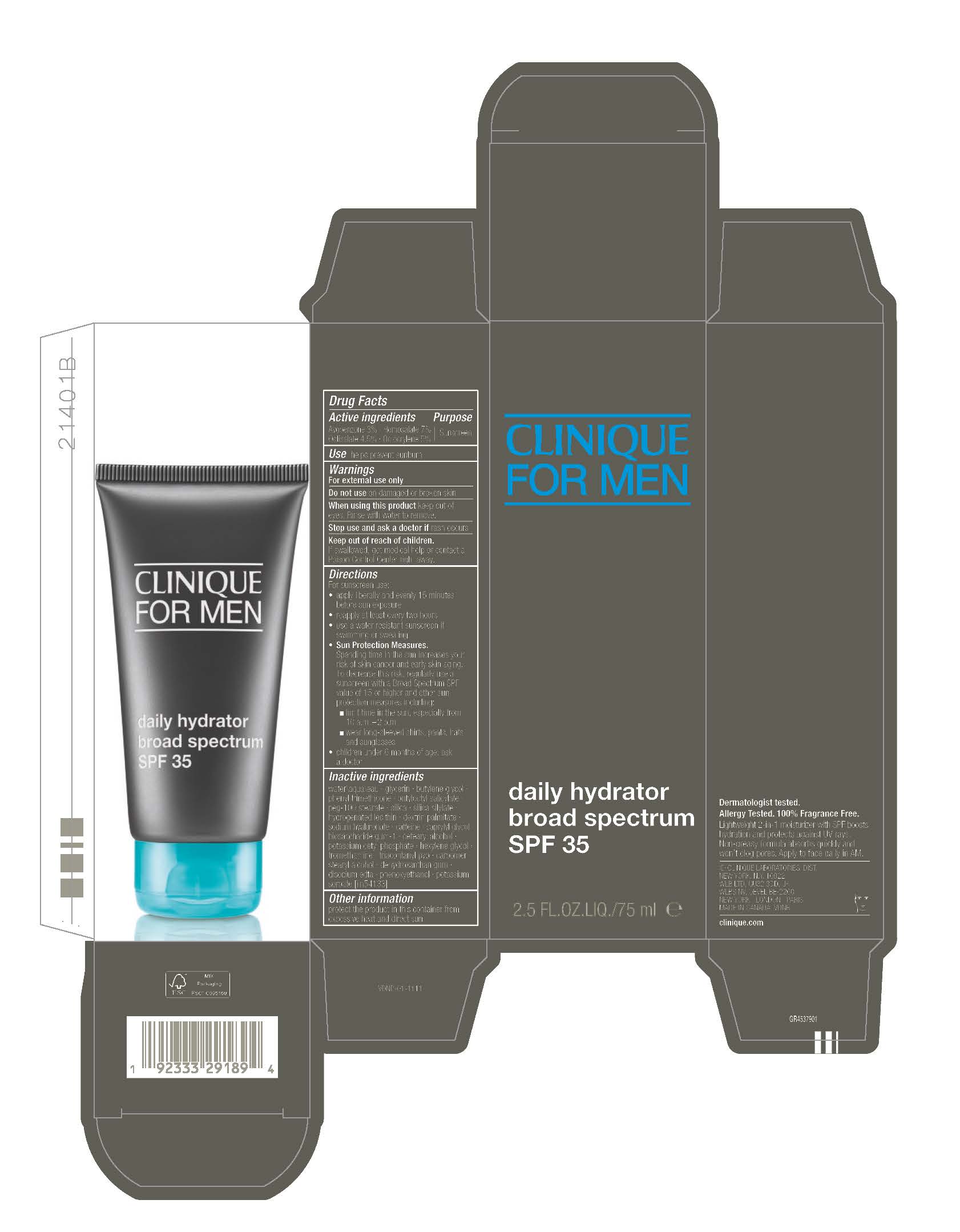 DRUG LABEL: CLINIQUE FOR MEN DAILY HYDRATOR BROAD SPECTRUM SPF 35
NDC: 49527-223 | Form: CREAM
Manufacturer: CLINIQUE LABORATORIES LLC
Category: otc | Type: HUMAN OTC DRUG LABEL
Date: 20251202

ACTIVE INGREDIENTS: OCTOCRYLENE 50 mg/1 mL; HOMOSALATE 70 mg/1 mL; OCTISALATE 45 mg/1 mL; AVOBENZONE 30 mg/1 mL
INACTIVE INGREDIENTS: CAFFEINE; HYDROGENATED SOYBEAN LECITHIN; SODIUM HYALURONATE; CETEARYL ALCOHOL; POTASSIUM CETYL PHOSPHATE; TROMETHAMINE; PEG-100 STEARATE; HEXYLENE GLYCOL; TRIACONTANYL PVP; SILICA; WATER; GLYCERIN; CAPRYLYL GLYCOL; CARBOMER; STEARYL ALCOHOL; BUTYLOCTYL SALICYLATE; BUTYLENE GLYCOL; DEHYDROXANTHAN GUM; PHENYL TRIMETHICONE; DEXTRIN PALMITATE (CORN; 20000 MW); BIOSACCHARIDE GUM-1; EDETATE DISODIUM ANHYDROUS; PHENOXYETHANOL; POTASSIUM SORBATE

CLINIQUE FOR MEN DAILY HYDRATOR BROAD SPECTRUM SPF 35

Active ingredients

AVOBENZONE 3%
HOMOSALATE 7%
OCTISALATE 4.5%
OCTOCRYLENE 5%

Purpose

Sunscreen

Use

helps prevent sunburn

Warnings

For external use only

Do not use on damaged or bronken skin

WHEN USING

Whn using this product keep out of eyes. Rinse with water to remove

Stop use and ask a doctor if rash occurs

Keep out of reach of children If swallowed, get medical help or contact a Poison Control Center right away

Directions

For sunscreen use:

- apply liberally 15 minutes before sun exposure
- reapply at least every two hours
- use a water resistant sunscreen if swimming or sweating
- Sun Protection Measures.
  Spending time in the sun increases your risk of skin cancer and early skin aging. To decrease this risk, regularly use a sunscreen with a Broad Spectrum SPF value of 15 or higher and other sun protection measures including:
  - limit time in the sun, especially from 10 a.m.–2 p.m.
  - wear long-sleeved shirts, pants, hats and sunglasses
- children under 6 months of age: ask a doctor

Inactive ingredients

WATER\AQUA\EAU,GLYCERIN,BUTYLENE GLYCOL,PHENYL TRIMETHICONE,BUTYLOCTYL SALICYLATE,PEG-100 STEARATE,SILICA,SILICA SILYLATE,HYDROGENATED LECITHIN,DEXTRIN PALMITATE,SODIUM HYALURONATE,CAFFEINE,CAPRYLYL GLYCOL,BIOSACCHARIDE GUM-1,CETEARYL ALCOHOL,POTASSIUM CETYL PHOSPHATE,HEXYLENE GLYCOL,TROMETHAMINE,TRIACONTANYL PVP,CARBOMER,STEARYL ALCOHOL,DEHYDROXANTHAN GUM,DISODIUM EDTA,PHENOXYETHANOL,POTASSIUM SORBATE <ILN54133>

Other information

protect the product in this container from excessive heat and direct sun

PACKAGE LABEL

CLINIQUE
FOR MEN
daily hydrator
braod spectrum
SPF 35
2.5 FL.OZ.LIQ./75ml e